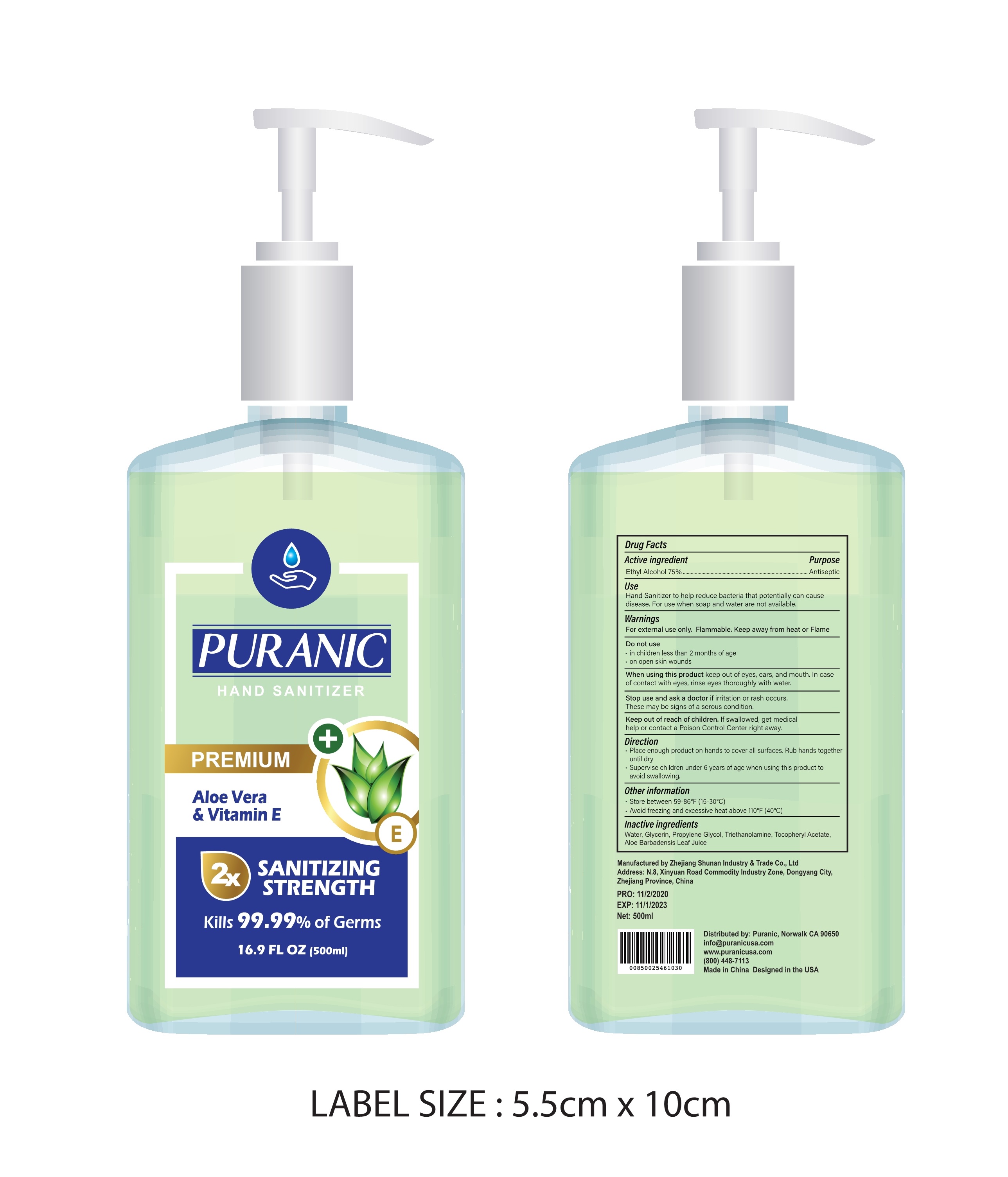 DRUG LABEL: Hand Sanitizer
NDC: 75556-502 | Form: GEL
Manufacturer: ZHEJIANG SHUNAN INDUSTRY&TRADE CO.,LTD
Category: otc | Type: HUMAN OTC DRUG LABEL
Date: 20201103

ACTIVE INGREDIENTS: ALCOHOL 375 mL/500 mL
INACTIVE INGREDIENTS: TROLAMINE; .ALPHA.-TOCOPHEROL ACETATE; GLYCERIN; PROPYLENE GLYCOL; WATER; ALOE VERA LEAF

75556-502 500 ml shunan 11754-500 Puranic, Inc

Active Ingredient(s)

Alcohol 75% v/v. Purpose: Antiseptic

Purpose

Antiseptic, Hand Sanitizer

Use

Hand Sanitizer to help reduce bacteria that potentially can cause disease. For use when soap and water are not available.

Warnings

For external use only. Flammable. Keep away from heat or flame

Do not use

- in children less than 2 months of age
- on open skin wounds

When using this product keep out of eyes, ears, and mouth. In case of contact with eyes, rinse eyes thoroughly with water.

Stop use and ask a doctor if irritation or rash occurs. These may be signs of a serious condition.

Keep out of reach of children. If swallowed, get medical help or contact a Poison Control Center right away.

Directions

- Place enough product on hands to cover all surfaces. Rub hands together until dry.
- Supervise children under 6 years of age when using this product to avoid swallowing.

Other information

- Store between 59-86℉(15-30℃)
- Avoid freezing and excessive heat above 110℉(40℃)

Inactive ingredients

Water,Glycerin,Propylene Glycol, Triethanolamine,Tocopheryl Acetate,Aloe Barbadensis Leaf Juice

Package Label - Principal Display Panel

500 mL in 1 Bottle NDC: 75556-502-01